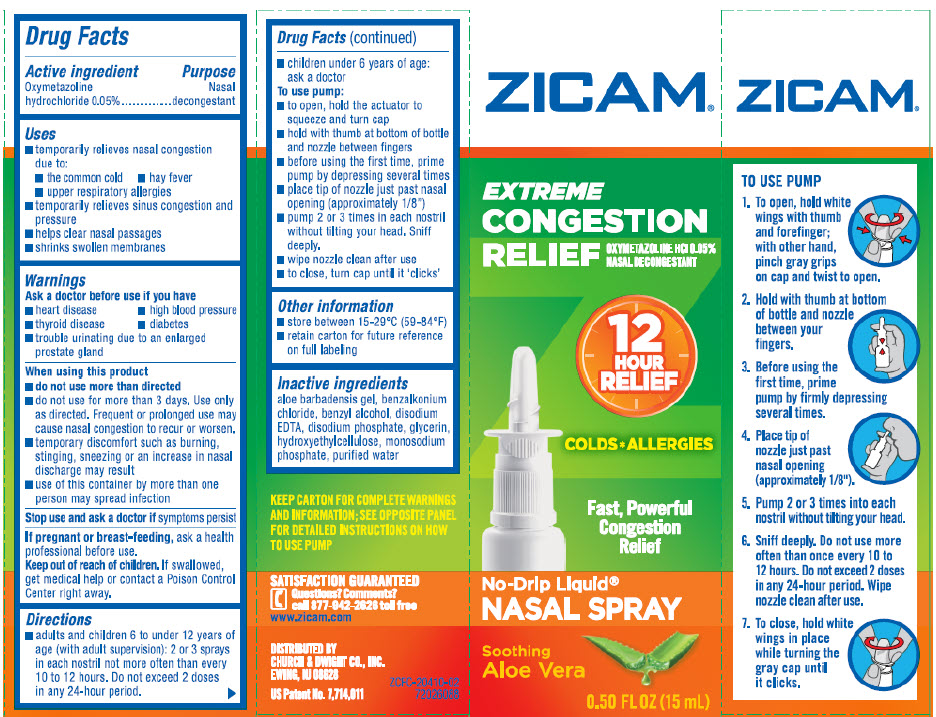 DRUG LABEL: Zicam Extreme Congestion Relief
NDC: 10237-464 | Form: SPRAY
Manufacturer: Church & Dwight Co., Inc.
Category: otc | Type: HUMAN OTC DRUG LABEL
Date: 20251231

ACTIVE INGREDIENTS: OXYMETAZOLINE HYDROCHLORIDE 0.5 mg/1 mL
INACTIVE INGREDIENTS: ALOE VERA LEAF; BENZALKONIUM CHLORIDE; BENZYL ALCOHOL; EDETATE DISODIUM; SODIUM PHOSPHATE, DIBASIC, ANHYDROUS; GLYCERIN; HYDROXYETHYL CELLULOSE (100 MPA.S AT 2%); SODIUM PHOSPHATE, MONOBASIC, UNSPECIFIED FORM; WATER

Zicam®Extreme Congestion Relief Nasal Spray

Active ingredient

Oxymetazoline hydrochloride 0.05%

Purpose

Nasal decongestant

Uses

- temporarily relieves nasal congestion due to:
  - the common cold
  - hay fever
  - upper respiratory allergies
- temporarily relieves sinus congestion and pressure
- helps clear nasal passages
- shrinks swollen membranes

Warnings

Ask a doctor before use if you have

- heart disease
- high blood pressure
- thyroid disease
- diabetes
- trouble urinating due to an enlarged prostate gland

When using this product

- do not use more than directed
- do not use for more than 3 days. Use only as directed. Frequent or prolonged use may cause nasal congestion to recur or worsen.
- temporary discomfort such as burning, stinging, sneezing or an increase in nasal discharge may result
- use of this container by more than one person may spread infection

Stop use and ask a doctor ifsymptoms persist

PREGNANCY OR BREAST FEEDING

If pregnant or breast-feeding,ask a health professional before use.

Keep out of reach of children.If swallowed, get medical help or contact a Poison Control Center right away.

Directions

- adults and children 6 to under 12 years of age (with adult supervision): 2 or 3 sprays in each nostril not more often than every 10 to 12 hours. Do not exceed 2 doses in any 24-hour period.
- children under 6 years of age: ask a doctor

To use pump:

- to open, hold the actuator to squeeze and turn cap
- hold with thumb at bottom of bottle and nozzle between fingers
- before using the first time, prime pump by depressing several times
- place tip of nozzle just past nasal opening (approximately 1/8")
- pump 2 or 3 times in each nostril without tilting your head. Sniff deeply.
- wipe nozzle clean after use
- to close, turn cap until it 'clicks'

Inactive ingredients

aloe barbadensis gel, benzalkonium chloride, benzyl alcohol, disodium EDTA, disodium phosphate, glycerin, hydroxyethylcellulose, monosodium phosphate, purified water

Questions? Comments?

call 877-942-2626 toll free

www.zicam.com

PRINCIPAL DISPLAY PANEL - 15 mL Bottle Carton

ZICAM®

EXTREME
CONGESTION
RELIEF

OXYMETAZOLINE HCl 0.05%
NASAL DECONGESTANT

12
HOUR
RELIEF

COLDS*ALLERGIES

Fast, Powerful
Congestion
Relief

No-Drip Liquid®
NASAL SPRAY

Soothing
Aloe Vera

0.50 FL OZ (15 mL)